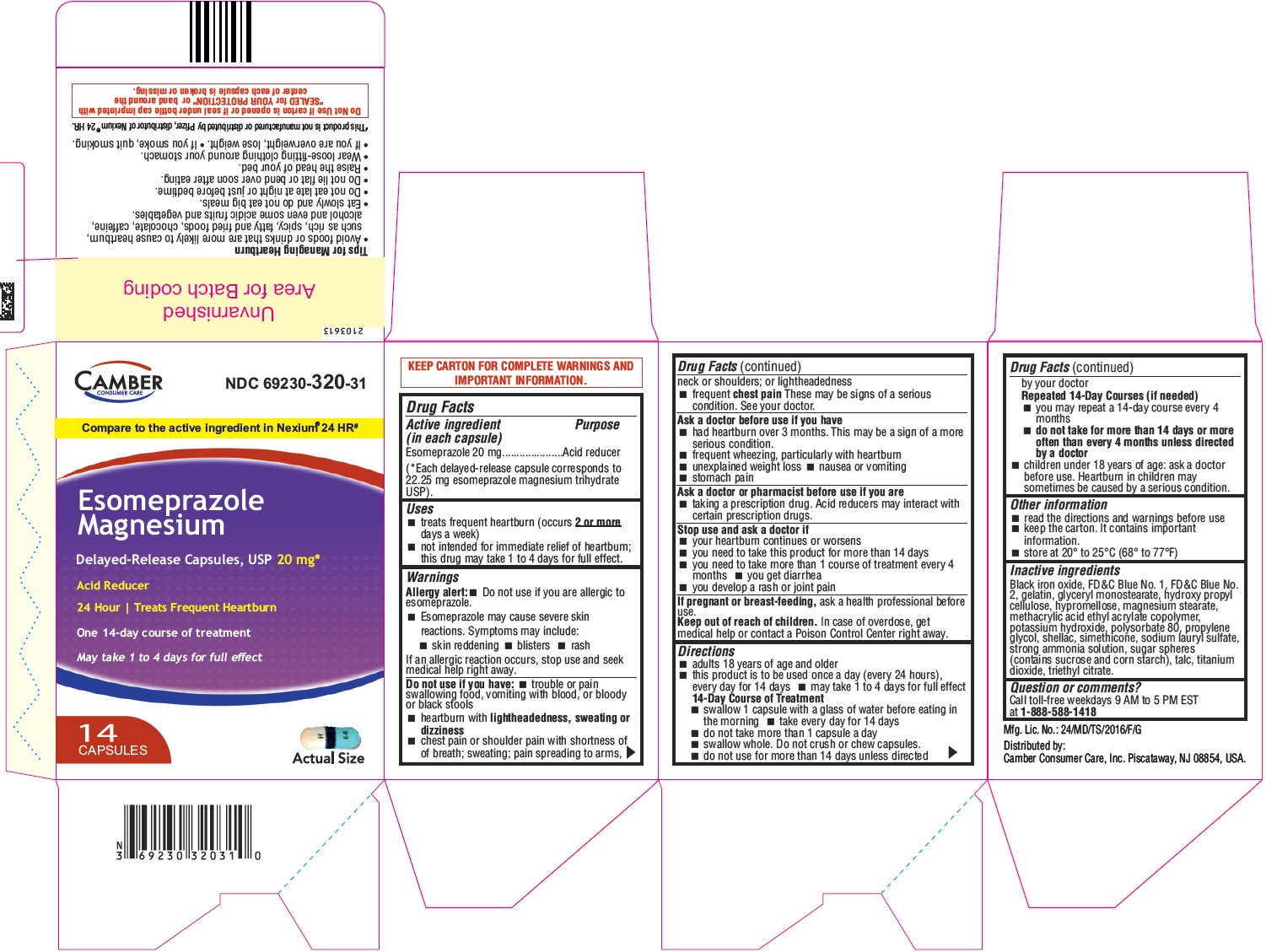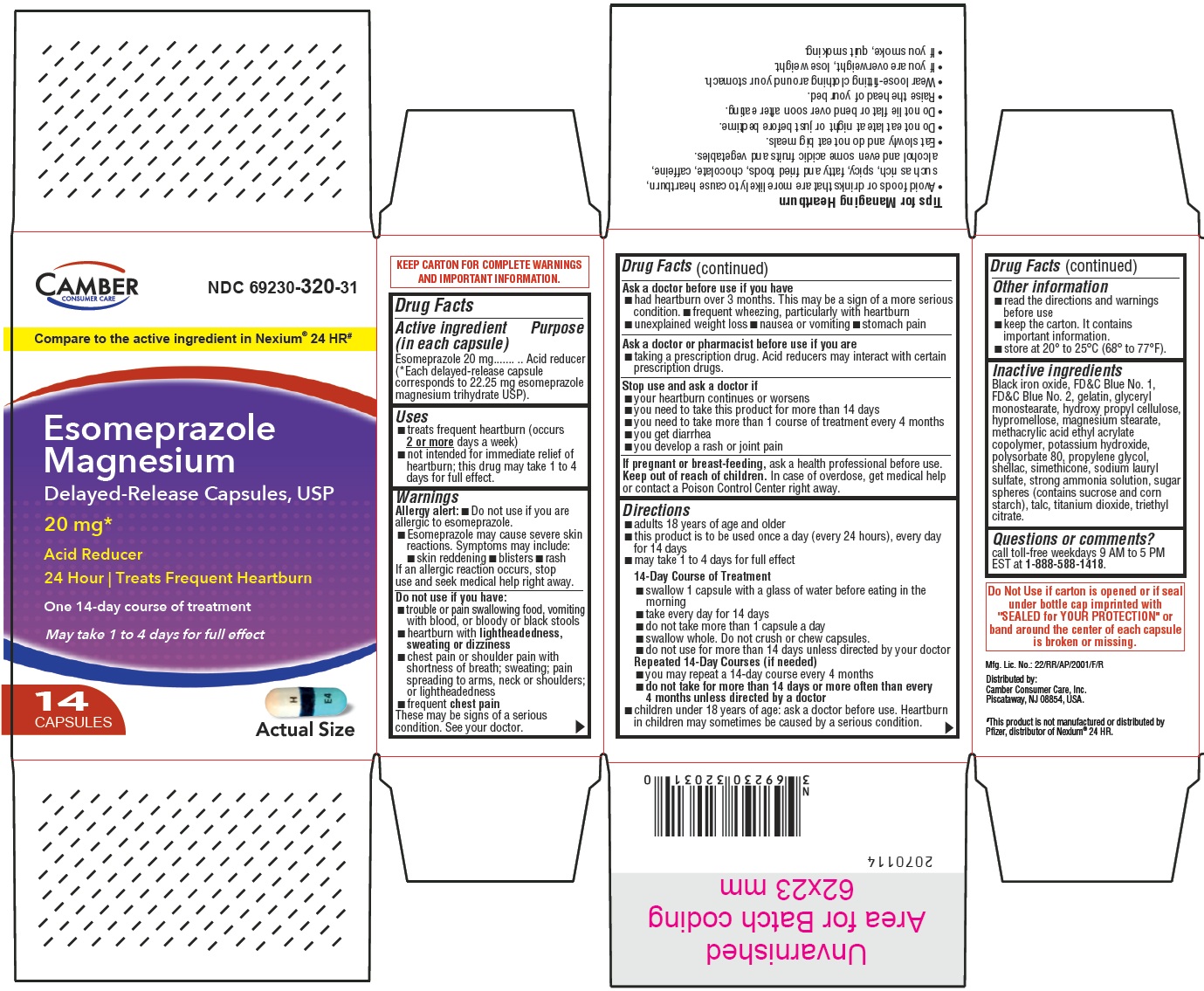 DRUG LABEL: Esomeprazole Magnesium

NDC: 69230-320 | Form: CAPSULE, DELAYED RELEASE
Manufacturer: Camber Consumer Care Inc
Category: otc | Type: HUMAN OTC DRUG LABEL
Date: 20250405

ACTIVE INGREDIENTS: ESOMEPRAZOLE MAGNESIUM 20 mg/1 1
INACTIVE INGREDIENTS: TALC; TRIETHYL CITRATE; FERROSOFERRIC OXIDE; FD&C BLUE NO. 1; FD&C BLUE NO. 2; GELATIN; GLYCERYL MONOSTEARATE; MAGNESIUM STEARATE; POTASSIUM HYDROXIDE; POLYSORBATE 80; PROPYLENE GLYCOL; SHELLAC; SODIUM LAURYL SULFATE; SUCROSE; HYDROXYPROPYL CELLULOSE; AMMONIA; STARCH, CORN; TITANIUM DIOXIDE; DIMETHICONE; METHACRYLIC ACID - ETHYL ACRYLATE COPOLYMER (1:1) TYPE A; HYPROMELLOSE 2910 (5 MPA.S)

Esomeprazole Magnesium Delayed-Release Capsules USP, 20 mg (OTC)

ACTIVE INGREDIENT (in each capsule)

Esomeprazole 20 mg
(*Each delayed-release capsule corresponds to 22.25 mg esomeprazole magnesium trihydrate USP).

PURPOSE

Acid reducer

USES

- treats frequent heartburn (occurs 2 or moredays a week)
- not intended for immediate relief of heartburn; this drug may take 1 to 4 days for full effect.

WARNINGS

Allergy alert:

- Do not use if you are allergic to esomeprazole.
- Esomeprazole may cause severe skin reactions. Symptoms may include:
- skin reddening . blisters .rash
  If an allergic reaction occurs, stop use and seek medical help right away.

DO NOT USE IF YOU HAVE

- trouble or pain swallowing food, vomiting with blood, or bloody or black stools
- heartburn with lightheadedness, sweating or dizziness
- chest pain or shoulder pain with shortness of breath; sweating; pain spreading to arms, neck or shoulders; or lightheadedness
- frequent chest pain.

These may be signs of a serious condition. See your doctor.

ASK A DOCTOR BEFORE USE IF YOU HAVE

- had heartburn over 3 months. This may be a sign of a more serious condition.
- frequent wheezing, particularly with heartburn
- unexplained weight loss
- nausea or vomiting
- stomach pain

ASK A DOCTOR OR PHARMACIST BEFORE USE IF YOU ARE

- taking a prescription drug. Acid reducers may interact with certain prescription drugs.

STOP USE AND ASK A DOCTOR IF

- your heartburn continues or worsens
- you need to take this product for more than 14 days
- you need to take more than 1 course of treatment every 4 months
- you get diarrhea
- you develop a rash or joint pain

IF PREGNANT OR BREAST-FEEDING

ask a health professional before use.

KEEP OUT OF REACH OF CHILDREN

In case of overdose, get medical help or contact a Poison Control Center right away.

DIRECTIONS

• adults 18 years of age and older
• this product is to be used once a day (every 24 hours), every day for 14 days
• may take 1 to 4 days for full effect

14-Day course of Treatment
• swallow 1 capsule with a glass of water before eating in the morning
• take every day for 14 days
• do not take more than 1 capsule a day
• swallow whole. Do not crush or chew capsules.
• do not use for more than 14 days unless directed by your doctor

Repeated 14-Day Courses (if needed)
• you may repeat a 14-day course every 4 months
• do not take for more than 14 days or more often than every 4 months unless directed by a doctor

• children under 18 years of age: ask a doctor before use. Heartburn in children may sometimes be caused by a serious condition.

OTHER INFORMATION

- read the directions and warnings before use
- keep the carton. It contains important information.
- store at 20° to 25°C (68° to 77°F)

INACTIVE INGREDIENTS

Black iron oxide, FD&C Blue No. 1, FD&C Blue No. 2, gelatin, glyceryl monostearate, hydroxy propyl cellulose, hypromellose, magnesium stearate, methacrylic acid ethyl acrylate copolymer, potassium hydroxide, polysorbate 80, propylene glycol, shellac, simethicone, sodium lauryl sulfate, strong ammonia solution, sugar spheres (contains sucrose and corn starch), talc, titanium dioxide, triethyl citrate.

QUESTIONS OR COMMENTS?

call toll-free weekdays 9 AM to 5 PM EST at 1-888-588-1418.

Distributed by:
Camber Consumer Care, Inc.

Piscataway, NJ 08854, USA.

PRINCIPAL DISPLAY PANEL

Esomeprazole Magnesium Delayed-Release Capsules, USP, 20 mg - Carton (Hetero)

Esomeprazole Magnesium Delayed-Release Capsules, USP, 20 mg - Carton (Annora)